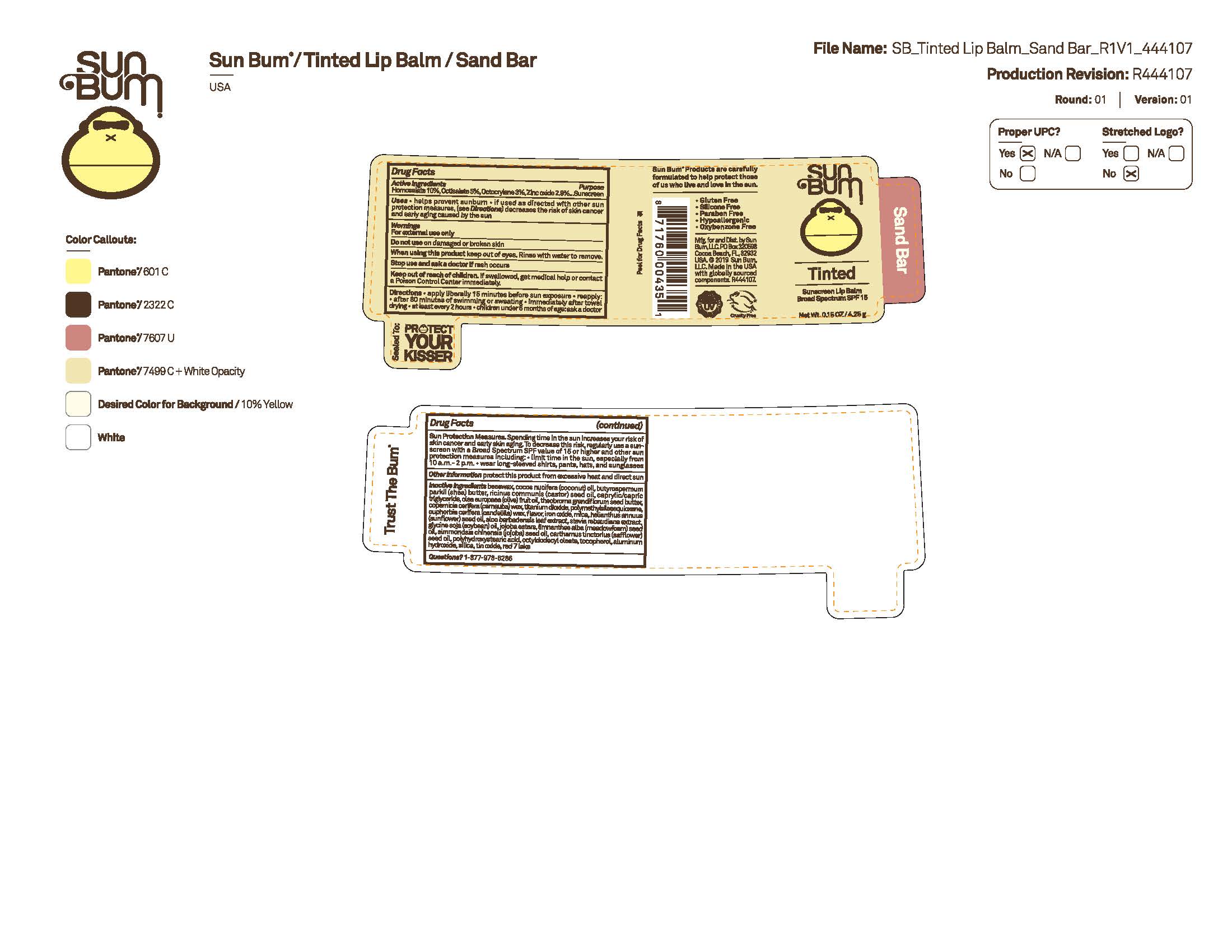 DRUG LABEL: Sun Bum Tinted Sunscreen Lip Balm Broad Spectrum SPF 15 - Sandbar
NDC: 69039-740 | Form: STICK
Manufacturer: Sun Bum, LLC
Category: otc | Type: HUMAN OTC DRUG LABEL
Date: 20250827

ACTIVE INGREDIENTS: HOMOSALATE 100 mg/1 g; ZINC OXIDE 29 mg/1 g; OCTOCRYLENE 30 mg/1 g; OCTISALATE 50 mg/1 g
INACTIVE INGREDIENTS: COPERNICIA CERIFERA (CARNAUBA) WAX; CARTHAMUS TINCTORIUS (SAFFLOWER) SEED OIL; RED 7; TOCOPHEROL; LIMNANTHES ALBA (MEADOWFOAM) SEED OIL; TIN OXIDE; BUTYROSPERMUM PARKII (SHEA) BUTTER; EUPHORBIA CERIFERA (CANDELILLA) WAX; MICA; HYDROLYZED JOJOBA ESTERS; ALUMINUM HYDROXIDE; SILICA; HELIANTHUS ANNUUS (SUNFLOWER) SEED OIL; SIMMONDSIA CHINENSIS (JOJOBA) SEED OIL; BEESWAX; RICINUS COMMUNIS (CASTOR) SEED OIL; THEOBROMA GRANDIFLORUM SEED BUTTER; TITANIUM DIOXIDE; STEVIA REBAUDIUNA LEAF; COCOS NUCIFERA (COCONUT) OIL; OCTYLDODECYL OLEATE; ALOE BARBADENSIS LEAF; SOYBEAN OIL; POLYHYDROXYSTEARIC ACID (2300 MW); POLYMETHYLSILSESQUIOXANE (4.5 MICRONS); OLEA EUROPAEA (OLIVE) FRUIT OIL; CAPRYLIC/CAPRIC TRIGLYCERIDE; FERRIC OXIDE RED

Sun Bum Tinted Sunscreen Lip Balm Broad Spectrum SPF 15 - Sandbar

Active Ingredients

HOMOSALATE 10%, OCTISALATE 5%, OCTOCRYLENE 3%, ZINC OXIDE 2.9%

Purpose

Sunscreen

Uses

• helps prevent sunburn • if used as directed with other sun protection measures, (see Directions) decreases the risk of skin cancer and early skin aging caused by the sun

Warnings

For external use only

Do not use on damaged or broken skin

When using this product keep out of eyes. Rinse with water to remove.

Stop use and ask a doctor if rash occurs

Keep out of reach of children. If swallowed, get medical help or contact a Poison Control Center immediately.

Warnings

Keep Out Of Reach Of Children

Directions

• apply liberally 15 minutes before sun exposure

• reapply: • after 80 minutes of swimming or sweating • immediately after towel drying • at least every 2 hours

• children under 6 months of age: ask a doctor

• Sun Protection Measures. Spending time in the sun increases your risk of skin cancer and early skin aging. To decrease this risk, regularly use a sunscreen with a Broad Spectrum SPF value of 15 or higher and other sun protection measures including:

• limit time in the sun, especially from 10 a.m.- 2 p.m.

• wear long-sleeved shirts, pants, hats and sunglasses

Directions

• apply liberally 15 minutes before sun exposure

Other Information

protect this product from excessive heat and direct sun

Inactive Ingredients

Beeswax, Cocos Nucifera (Coconut) Oil, Butyrospermum Parkii (Shea) Butter, Ricinus Communis (Castor) Seed Oil, Caprylic/Capric Triglyceride, Olea Europaea (Olive) Fruit Oil, Theobroma Grandiflorum Seed Butter, Copernicia Cerifera (Carnauba) Wax, Titanium Dioxide, Polymethylsilsesquioxane, Euphorbia Cerifera (Candelilla) Wax, Flavor, Iron Oxides, Mica, Helianthus Annuus (Sunflower) Seed Oil, Aloe Barbadensis Leaf Extract, Stevia Rebaudiana Extract, Glycine Soja (Soybean) Oil, Jojoba Esters, Limnanthes Alba (Meadowfoam) Seed Oil, Simmondsia Chinensis (Jojoba) Seed Oil, Carthamus Tinctorius (Safflower) Seed Oil, Polyhydroxystearic Acid, Octyldodecyl Oleate, Tocopherol, Aluminum Hydroxide, Silica, Tin Oxide, Red 7 Lake

Questions?

1-877-978-6286